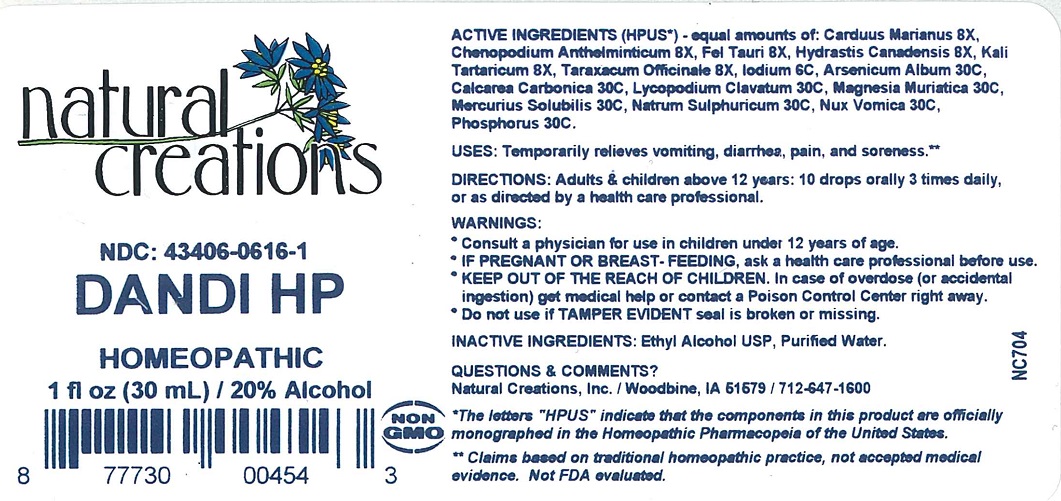 DRUG LABEL: DANDI HP
NDC: 43406-0616 | Form: LIQUID
Manufacturer: Natural Creations, Inc.
Category: homeopathic | Type: HUMAN OTC DRUG LABEL
Date: 20251208

ACTIVE INGREDIENTS: MILK THISTLE 8 [hp_X]/1 mL; DYSPHANIA AMBROSIOIDES 8 [hp_X]/1 mL; BOS TAURUS BILE 8 [hp_X]/1 mL; GOLDENSEAL 8 [hp_X]/1 mL; POTASSIUM TARTRATE HEMIHYDRATE 8 [hp_X]/1 mL; TARAXACUM OFFICINALE 8 [hp_X]/1 mL; IODINE 6 [hp_C]/1 mL; ARSENIC TRIOXIDE 30 [hp_C]/1 mL; OYSTER SHELL CALCIUM CARBONATE, CRUDE 30 [hp_C]/1 mL; LYCOPODIUM CLAVATUM SPORE 30 [hp_C]/1 mL; MAGNESIUM CHLORIDE 30 [hp_C]/1 mL; MERCURIUS SOLUBILIS 30 [hp_C]/1 mL; SODIUM SULFATE 30 [hp_C]/1 mL; STRYCHNOS NUX-VOMICA SEED 30 [hp_C]/1 mL; PHOSPHORUS 30 [hp_C]/1 mL
INACTIVE INGREDIENTS: ALCOHOL; WATER

DANDI HP

ACTIVE INGREDIENT

ACTIVE INGREDIENTS (HPUS*) - equal amounts of: Carduus Marianus 8X, Chenopodium Anthelminticum 8X, Fel Tauri 8X, Hydrastis Canadensis 8X, Kali Tartaricum 8X, Taraxacum Officinale 8X, Iodium 6C, Arsenicum Album 30C, Calcarea Carbonica 30C, Lycopodium Clavatum 30C, Magnesia Muriatica 30C, Mercurius Solubilis 30C, Natrum Sulphuricum 30C, Nux Vomica 30C, Phosphorus 30C.

PURPOSE

USES: Temporarily relieves vomiting, diarrhea, pain, and soreness.**

INDICATIONS AND USAGE

USES: Temporarily relieves vomiting, diarrhea, pain, and soreness.**

DOSAGE AND ADMINISTRATION

DIRECTIONS: Adults & children above 12 years: 10 drops orally 3 times daily, or as directed by a health care professional.

KEEP OUT OF REACH OF CHILDREN

KEEP OUT OF THE REACH OF CHILDREN. In case of overdose (or accidental ingestion) get medical help or contact a Poison Control Center right away

WARNINGS:

- Consult a physician for use in children under 12 years of age.
- IF PREGNANT OR BREAST-FEEDING, ask a health care professional before use.
- KEEP OUT OF THE REACH OF CHILDREN. In case of overdose (or accidental ingestion) get medical help or contact a Poison Control Center right away.
- Do not use if TAMPER EVIDENT seal is broken or missing.

INACTIVE INGREDIENTS: Ethyl Alcohol USP, Purified Water.

QUESTIONS & COMMENTS?

Natural Creations, Inc. / Woodbine, IA 51579 / 712-647-1600

REFERENCES

*The letters "HPUS" indicate that the components in this product are officially monographed in the Homeopahic Pharmacopeia of the United States.

**Claims beased on traditional homeopathic practice, not accepted medical evidence. Not FDA evaluated.

PACKAGE LABEL

NDC: 43406-0616-1

DANDI HP

HOMEOPATHIC

1 fl oz (30 mL) / 20% Alcohol